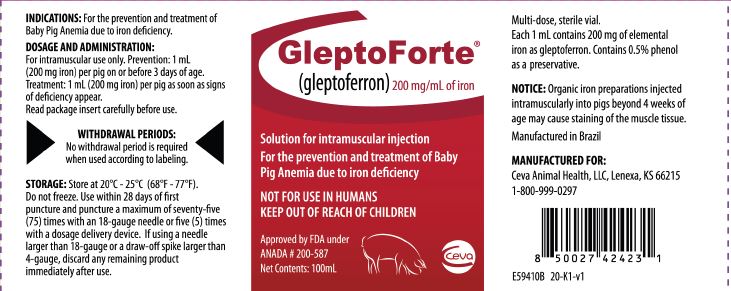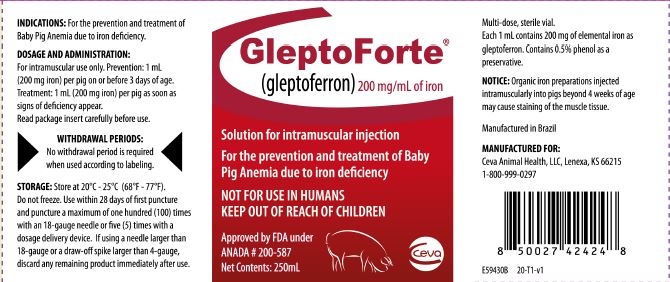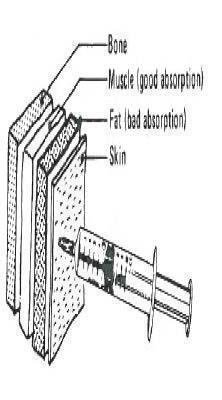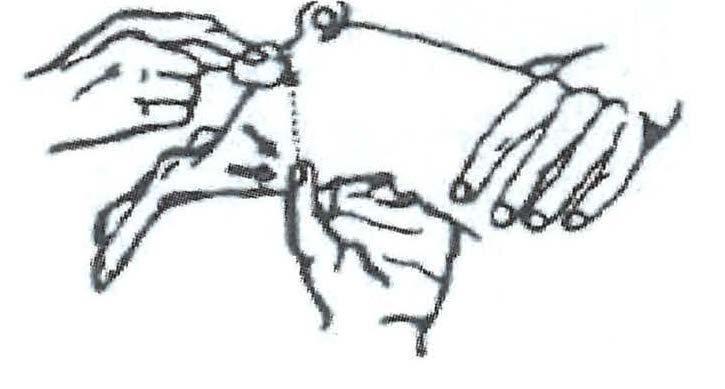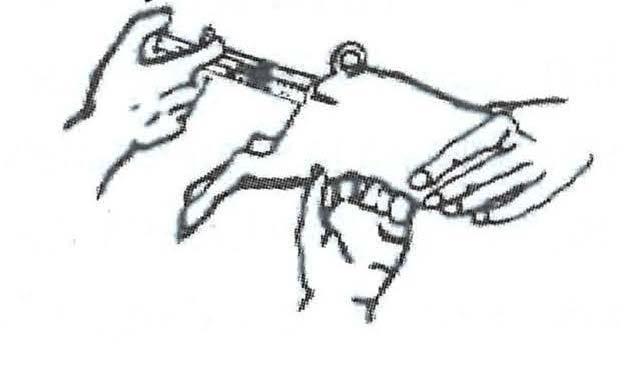 DRUG LABEL: GleptoForte
NDC: 13744-525 | Form: INJECTION
Manufacturer: Ceva Sante Animale
Category: animal | Type: OTC ANIMAL DRUG LABEL
Date: 20250814

ACTIVE INGREDIENTS: GLEPTOFERRON 200 mg/1 mL

DESCRIPTION

GleptoForte®

(gleptoferron)

200 mg/mL of iron

Solution for intramuscular injection

NOT FOR USE IN HUMANS

KEEP OUT OF REACH OF CHILDREN

Approved by FDA under ANADA # 200-587

DESCRIPTION

DESCRIPTION: GleptoForte® is a sterile aqueous colloidal solution of gleptoferron, a macromolecular complex of ferric hydroxide and dextran glucoheptonic acid. Each milliliter contains 200 mg of elemental iron. The solution contains 0.5% phenol as preservative.

MECHANISM OF ACTION

ACTIONS: GleptoForte® contains gleptoferron which provides a rapidly absorbed and readily utilizable form of iron for the prevention and treatment of baby pig anemia.

INDICATIONS AND USAGE

INDICATIONS: GleptoForte® is recommended for both the routine prevention and treatment of baby pig anemia due to iron deciency.

NOTICE: Organic iron preparations injected intramuscularly into pigs beyond 4 weeks of age may cause staining of the muscle tissue.

DOSAGE AND ADMINISTRATION: GleptoForte® is for intramuscular use only. Prevention: 1 mL (200 mg iron) per pig on or before 3 days of age. Treatment: 1 mL (200 mg iron) per pig as soon as signs of deficiency appear.

WITHDRAWAL PERIODS: No withdrawal period is required when used according to labeling.

ANIMAL SAFETY WARNINGS AND PRECAUTIONS: Occasionally pigs may show a reaction to injectable iron, clinically characterized by prostration with muscular weakness. In extreme cases, death may occur.

For a copy of the Safety Data Sheet (SDS) or to report suspected adverse drug events, contact CEVA at 1-800-999-0297.

For additional information about adverse drug experience reporting for animal drugs, contact FDA at 1-888-FDA-VETS or http://www.fda.gov/AnimalVeterinary/SafetyHealth.

HOW TO INJECT:

What to use

1. GleptoForte® (gleptoferron) injection

2. Ordinary 10 mL syringe with 18-guage needle or smaller, or dosage delivery device with 4-guage draw off spike or smaller

3. Disinfectant (rubbing alcohol or tincture of iodine)

Where to use:

GleptoForte® is for intramuscular use. The preferred site of injection is the ham muscle. Push the needle directly into the ham to approximately a one-half (1/2) inch depth. Avoid injection into a blood vessel. This is best avoided by pulling back slightly on the plunger after the needle is seated in the ham. If properly located, resistance will be offered to this effort. If the plunger is pulled back easily, remove and relocate the needle.

Step 1 The pig is held under-arm, between knees, or by an assistant. Disinfect the injection site. Pull down skin and fat with thumb as shown. Approximately halfway along a line between the anus and the thumb is the best injection site.

Step 2 Before injecting GleptoForte®, point the needle upward and gently press the plunger to expel all air from syringe. The needle is inserted at right-angle to the skin into the ham approximately a one-half (1/2) inch depth and the injection made.

Step 3 Use a new needle between each stopper puncture. Protect the needle from contamination and disinfect between animal injections.

HOW SUPPLIED:

GleptoForte® (gleptoferron) injection is available in 100 mL and 250 mL multi-dose vials.

STORAGE AND HANDLING

STORAGE: Store at 20°C - 25°C (68°F - 77°F). Do not freeze.

100 mL Vial: Use within 28 days of first puncture and puncture a maximum of seventy-five (75) times with an 18-guage needle or five (5) times with a dosage delivery device. If using a needle larger than 18-guage or a draw-off spike larger than 4-guage, discard any remaining product immediately ater use.

250 mL Vial: Use within 28 days of first puncture and puncture a maximum of one hundred (100) times with an 18-guage needle or five (5) times with a dosage delivery device. If using a needle larger than 18-guage or a draw-off spike larger than 4-guage, discard any remaining product immediately ater use.

Manufactured for:
Ceva Animal Health, LLC, Lenexa, KS 66215
1-800-999-0297

GleptoForte® is a registered trademark of Ceva Santé Animale

Principal Display Panel - 100 mL Bottle Label

GleptoForte®

(gleptoferron) 200 mg/mL of iron

Solution for intramuscular injection

For the prevention and treatment of Baby Pig Anemia due to iron deficiency

NOT FOR USE IN HUMANS

KEEP OUT OF REACH OF CHILDREN

Approved by FDA under ANADA # 200-587

Net Contents: 100mL

Principal Display Panel - 250 mL Bottle Label

GleptoForte®

(gleptoferron) 200 mg/mL of iron

Solution for intramuscular injection

For the prevention and treatment of Baby Pig Anemia due to iron deficiency

NOT FOR USE IN HUMANS

KEEP OUT OF REACH OF CHILDREN

Approved by FDA under ANADA # 200-587

Net Contents: 250mL